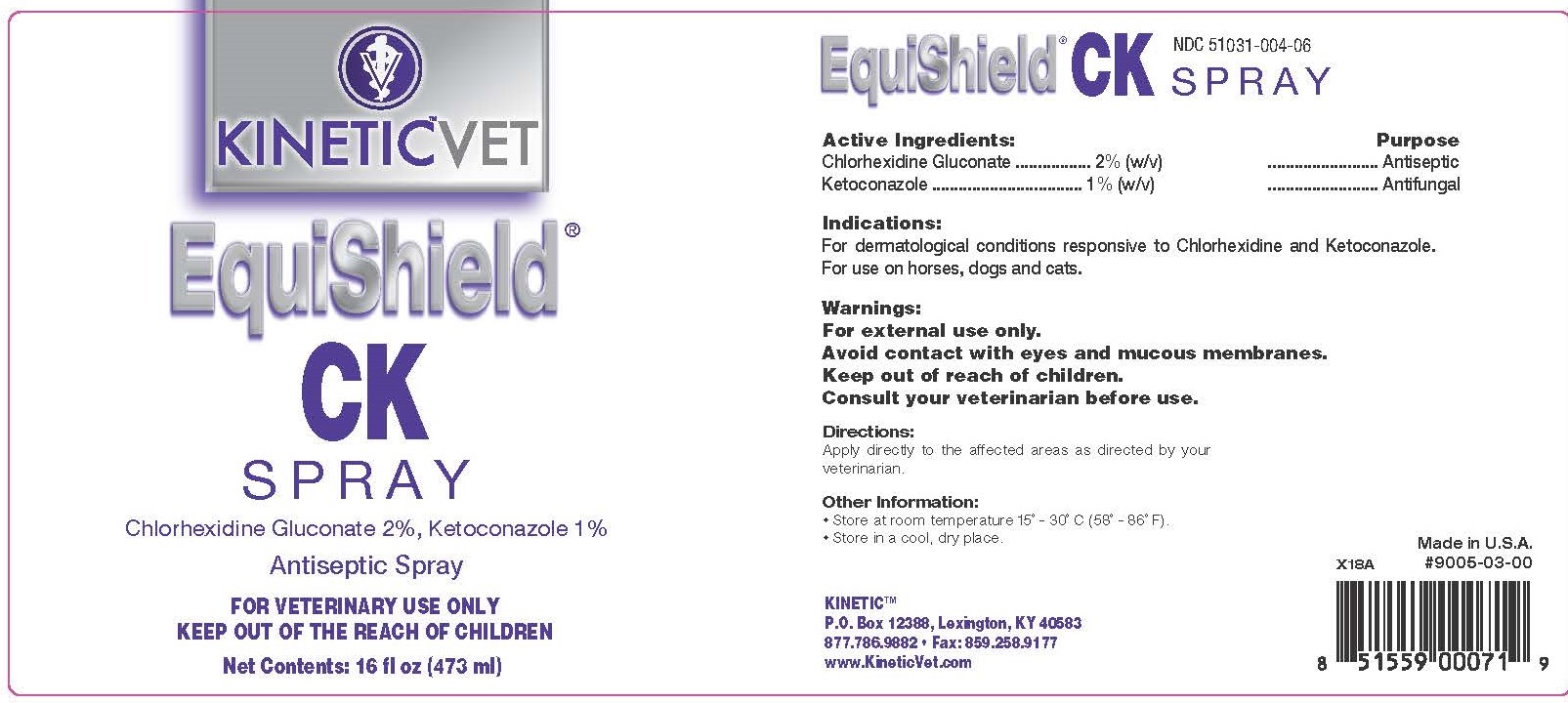 DRUG LABEL: EquiShield CK
NDC: 51031-004 | Form: SPRAY
Manufacturer: Kinetic Technologies, LLC
Category: animal | Type: OTC ANIMAL DRUG LABEL
Date: 20240313

ACTIVE INGREDIENTS: CHLORHEXIDINE GLUCONATE 2 g/100 mL; KETOCONAZOLE 1 g/100 mL

EquiShield CK Spray

Active Ingredients:

Chlorhexidine Gluconate 2% (w/v)
Ketoconazole 1% (w/v)

Purpose

Antiseptic
Antifungal

Indications:

For dermatological conditions responsive to Chlorhexidine and Ketoconazole. For use on horses, dogs and cats.

Warnings:

For external use only.

Avoid contact with eyes and mucous membranes.

Keep out of reach of children.

Consult your veterinarian before use.

Directions:

Apply directly to affected areas as directed by your veterinarian.

Other Information:

• Store at room temperature 15˚ - 30˚C (58˚ - 86˚F).
• Store in a cool, dry place.

PACKAGE LABEL

KINETIC™VET

EquiShield® CK Spray

Chlorhexidine Gluconate 2%, Ketaconazole 1%

Antiseptic Spray

FOR VETERINARY USE ONLY

KEEP OUT OF THE REACH OF CHILDREN

Net Contents: 16 fl oz (473 ml)